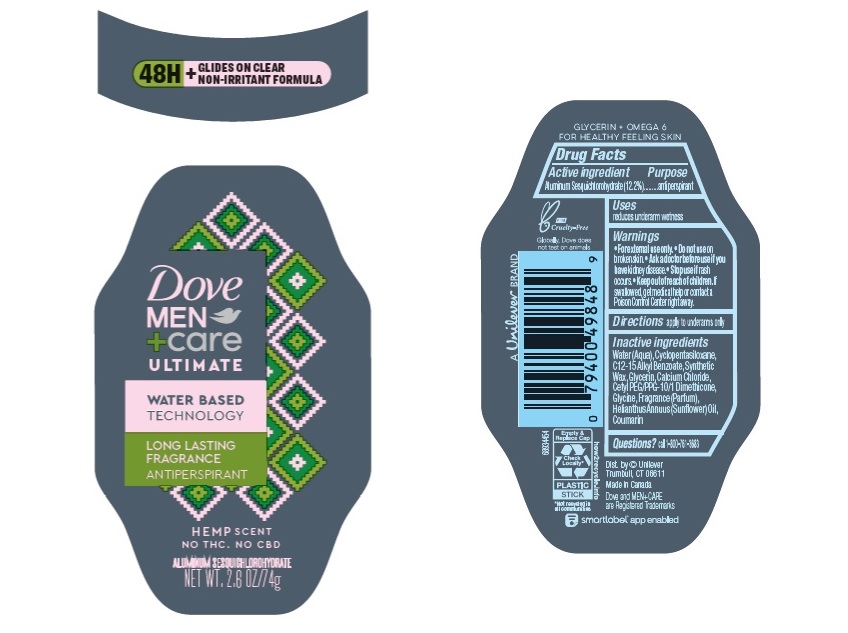 DRUG LABEL: Dove
NDC: 64942-2078 | Form: STICK
Manufacturer: Conopco Inc. d/b/a/ Unilever
Category: otc | Type: HUMAN OTC DRUG LABEL
Date: 20241106

ACTIVE INGREDIENTS: ALUMINUM SESQUICHLOROHYDRATE 12.2 g/100 g
INACTIVE INGREDIENTS: COUMARIN; GLYCINE; CYCLOMETHICONE 5; SUNFLOWER OIL; WATER; ALKYL (C12-15) BENZOATE; GLYCERIN; SYNTHETIC WAX (1200 MW); CALCIUM CHLORIDE; CETYL PEG/PPG-10/1 DIMETHICONE (HLB 2)

Dove Men + Care Ultimate Hemp Scent 48H Antiperspirant

Drug Facts

Active ingredient

Aluminum Sesquichlorohydrate (12.2 %)

Purpose

antiperspirant

Uses

reduces underarm wetness

Warnings

• For external use only.
• Do not use on broken skin .
• Ask a doctor before use if you have kidney disease.
• Stop use if rash occurs.

• Keep out of reach of children.

If swallowed, get medical help or contact a Poison Control Center right away.

Directions

apply to underarms only

Inactive ingredients

Water (Aqua), Cyclopentasiloxane, C12-15 Alkyl Benzoate, Synthetic Wax, Glycerin, Calcium Chloride, Cetyl PEG/PPG-10/1 Dimethicone, Glycine, Fragrance (Parfum), Helianthus Annuus (Sunflower) Oil, Coumarin

Questions?

Call 1-800-761-3683